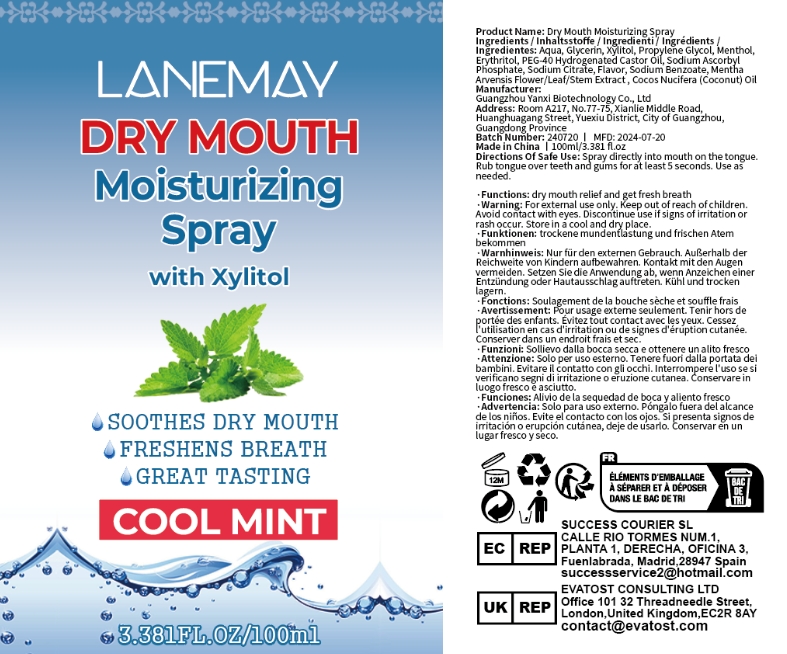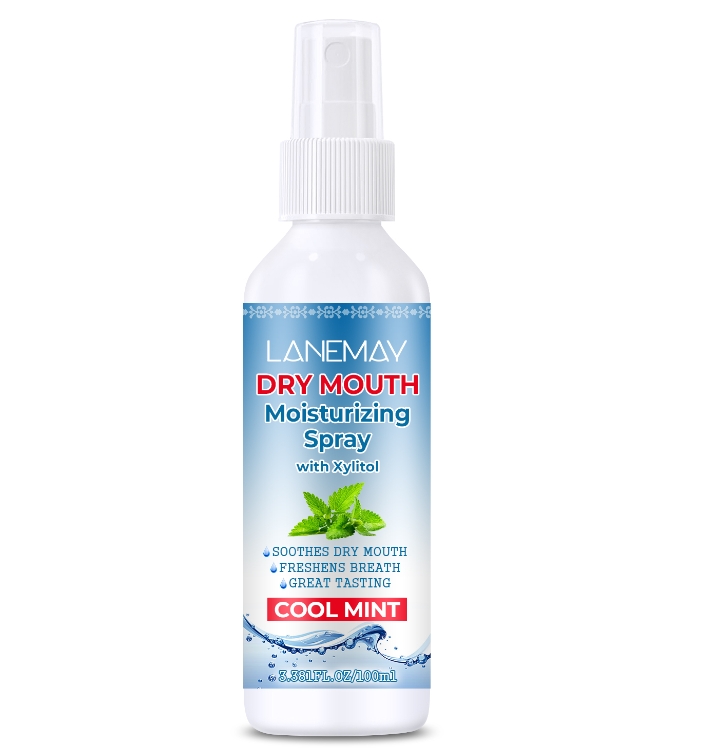 DRUG LABEL: Dry Mouth MoisturizingSpray
NDC: 84025-097 | Form: SPRAY
Manufacturer: Guangzhou Yanxi Biotechnology Co., Ltd
Category: otc | Type: HUMAN OTC DRUG LABEL
Date: 20240729

ACTIVE INGREDIENTS: XYLITOL 3 mg/100 mL; DIGLYCERIN 5 mg/100 mL
INACTIVE INGREDIENTS: WATER

DOSAGE AND ADMINISTRATION

Spray directly into mouth on the tongue

WARNINGS

Keep out of children

INACTIVE INGREDIENT

Aqua

INDICATIONS AND USAGE

dry mouth

keep out of children

PURPOSE

dry mouth relief and get fresh breath